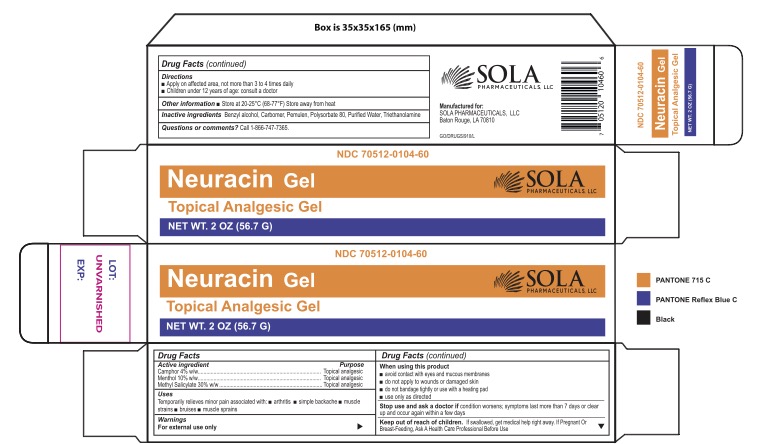 DRUG LABEL: Neuracin Topical Gel
NDC: 70512-104 | Form: GEL
Manufacturer: SOLA Pharmaceuticals
Category: otc | Type: HUMAN OTC DRUG LABEL
Date: 20251208

ACTIVE INGREDIENTS: METHYL SALICYLATE 300 mg/1 g; CAMPHOR (SYNTHETIC) 40 mg/1 g; MENTHOL, UNSPECIFIED FORM 100 mg/1 g
INACTIVE INGREDIENTS: BENZYL ALCOHOL; TROLAMINE; CARBOMER COPOLYMER TYPE A (ALLYL PENTAERYTHRITOL CROSSLINKED); CARBOMER 940; POLYSORBATE 80; WATER

Neuracin Topical Analgesic Gel

Active Ingredients

Camphor 4%

Menthol 10%

Methyl Salicylate 30%

Purpose

Topical Analgesic

Uses

Temporarily relieves minor pain associated with:

- Arthritis
- Simple Backache
- Muscle Strains
- Bruises
- Muscle Sprains

Warnings

For External use only

When using this product

- avoid contact with eyes and mucous membranes
- do no apply to wounds or damaged skin
- do not bandage tightly or use with a heating pad
- use only as directed

Stop use and ask a doctor if condition worsens; symptoms last more than 7 days or clear up and occur again within a few days

Keep out of reach of children. If swallowed, get medical help right away. If pregnant Or Breast-Feeding, Ask A Health Professional Before Use

Directions

- Apply on affected area, not more than 3 to 4 times daily
- Children under 12 years of age; consult a doctor

Other Information

- Store at 20-25ºC (68-77ºF) Store away from heat

Inactive Ingredients

Benzyl alcohol, Carbomer, Pemulen, Polysorbate 80, Purified Water, Triethanolamine

Questions or comments? Call 1-866-747-7365

Neuracin Topical Analgesic Gel

NDC 70512-104-60

Qty 2oz (56.7G)